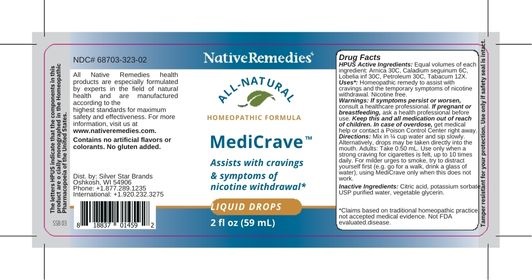 DRUG LABEL: MediCrave
NDC: 68703-323 | Form: LIQUID
Manufacturer: Silver Star Brands
Category: homeopathic | Type: HUMAN OTC DRUG LABEL
Date: 20250101

ACTIVE INGREDIENTS: DIEFFENBACHIA SEGUINE 6 [hp_C]/59 mL; LIQUID PETROLEUM 30 [hp_C]/59 mL; ARNICA MONTANA 30 [hp_C]/59 mL; LOBELIA INFLATA 30 [hp_C]/59 mL; TOBACCO LEAF 12 [hp_X]/59 mL
INACTIVE INGREDIENTS: WATER; GLYCERIN

NativeRemedies® MediCrave™

HPUS Active Ingredient: Equal volumes of each ingredient: Arnica 30C, Caladium seguinum 6C, Lobelia inf 30C, Petroleum 30C, Tabacum 12X.

The letters HPUS indicate that the components in this product are officially monographed in the Homeopathic Pharmacopoeia of the United States.

Uses*:

Uses*: Homeopathic remedy to assist with cravings and the temporary symptoms of nicotine withdrawal. Nicotine free.

*This statement has not been evaluated by the Food and Drug Administration. This product is not intended to diagnose, treat, cure or prevent any disease.

Warnings

Warnings: If symptoms persist or worsen, consult a healthcare professional. If pregnant or breastfeeding, ask a healthcare professional before use. Keep this and all medication out of reach of children. In case of overdose, get medical help or contact a Poison Control Center right away.

Directions

Directions: Mix in 1/4 cup water and sip slowly. Alternatively, drops may be taken directly into the mouth. Adults: Take 0.50 mL. Use only when a strong craving for cigarettes is felt, up to 10 times daily. For milder urges to smoke, try to distract yourself first (e.g. go for a walk, drink a glass of water), using MediCrave only when this does not work.

OTHER SAFETY INFORMATION

Contains no artificial flavors or colorants. No gluten added.

Tamper resistant for your protection. Use only if safety seal is intact.

Inactive Ingredients

Inactive Ingredients: USP purified water, Vegetable glycerin.

KEEP OUT OF REACH OF CHILDREN

Keep this and all medication out of reach of children.

PREGNANCY OR BREAST FEEDING

If pregnant or breastfeeding, ask a healthcare professional before use.

PURPOSE

Assists with cravings & symptoms of nicotine withdrawal*